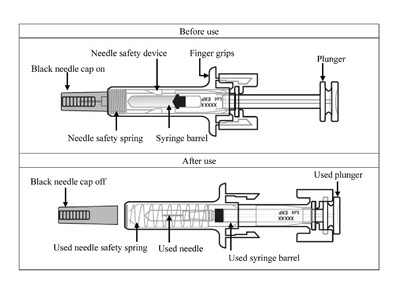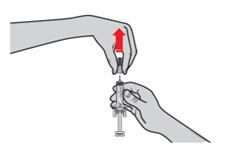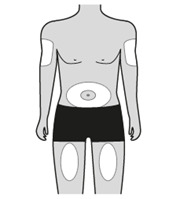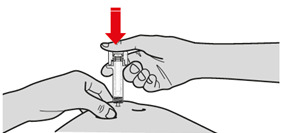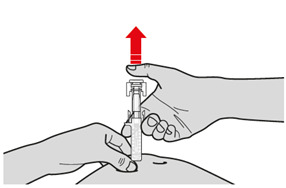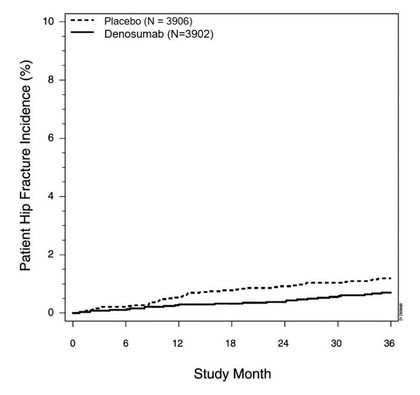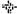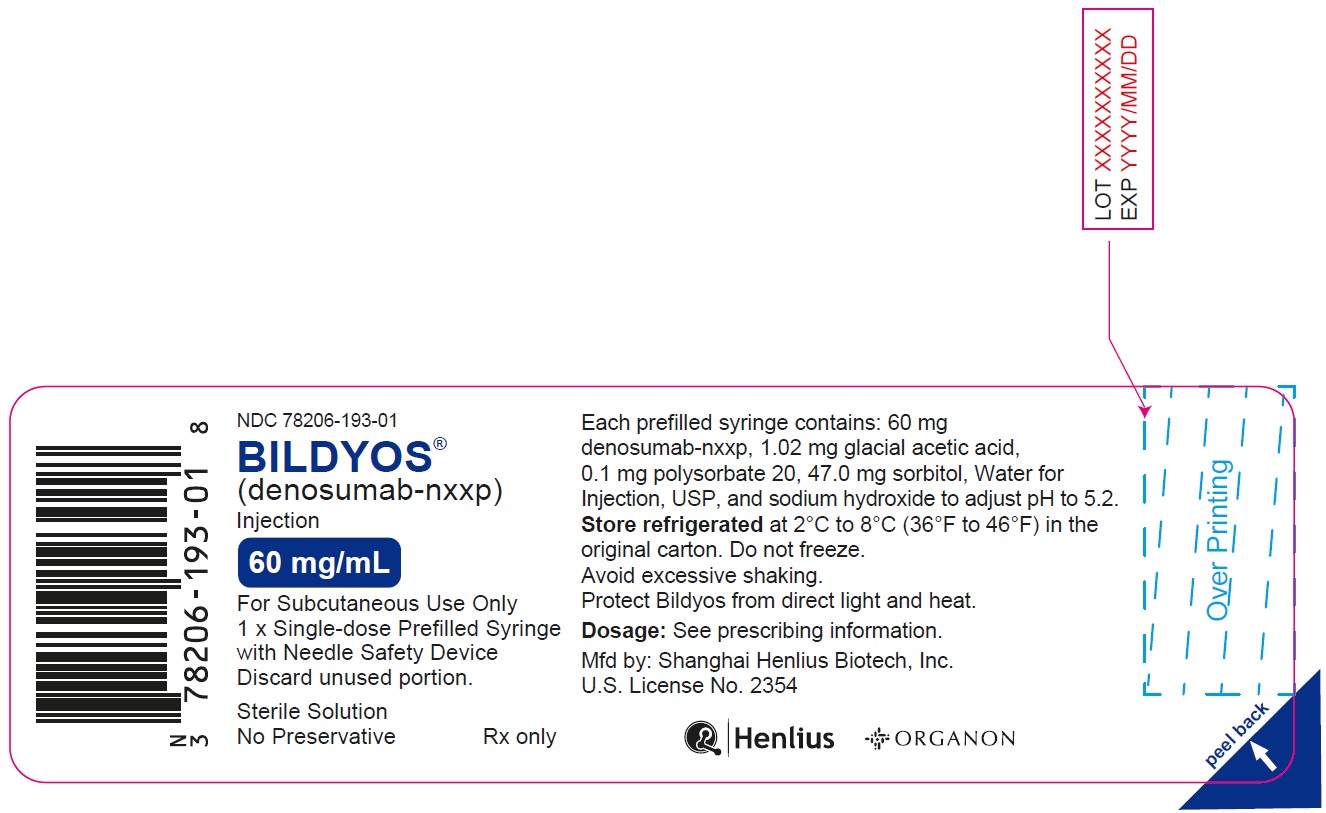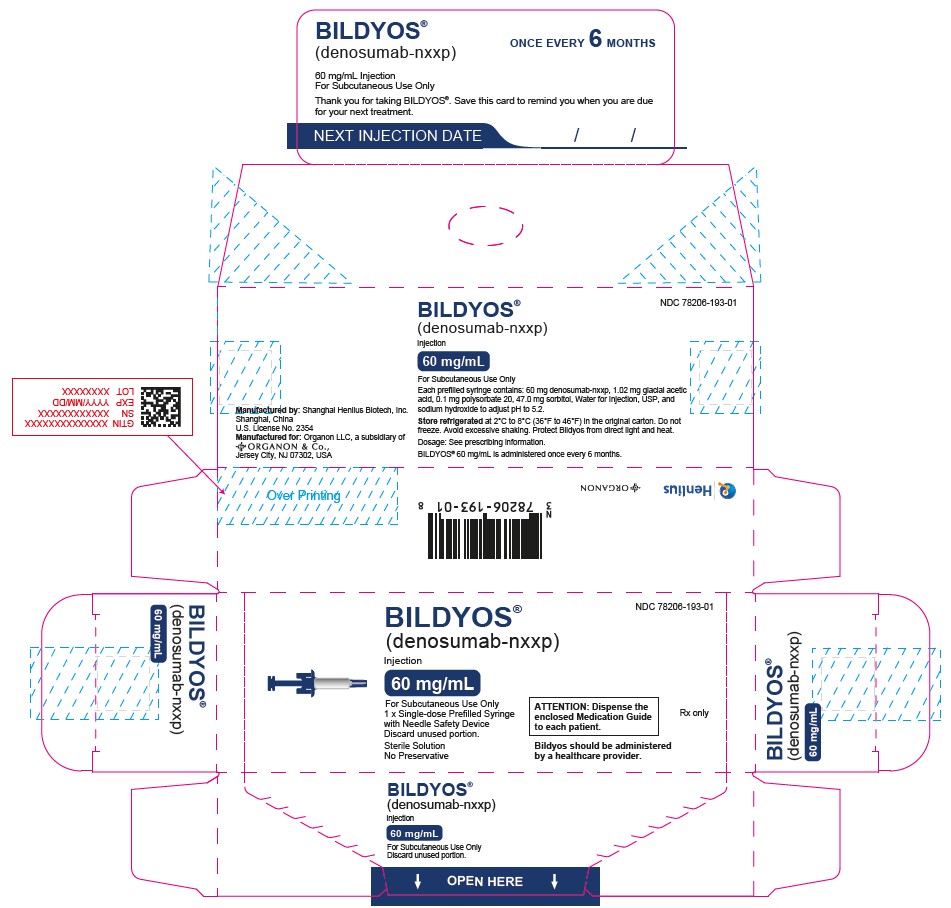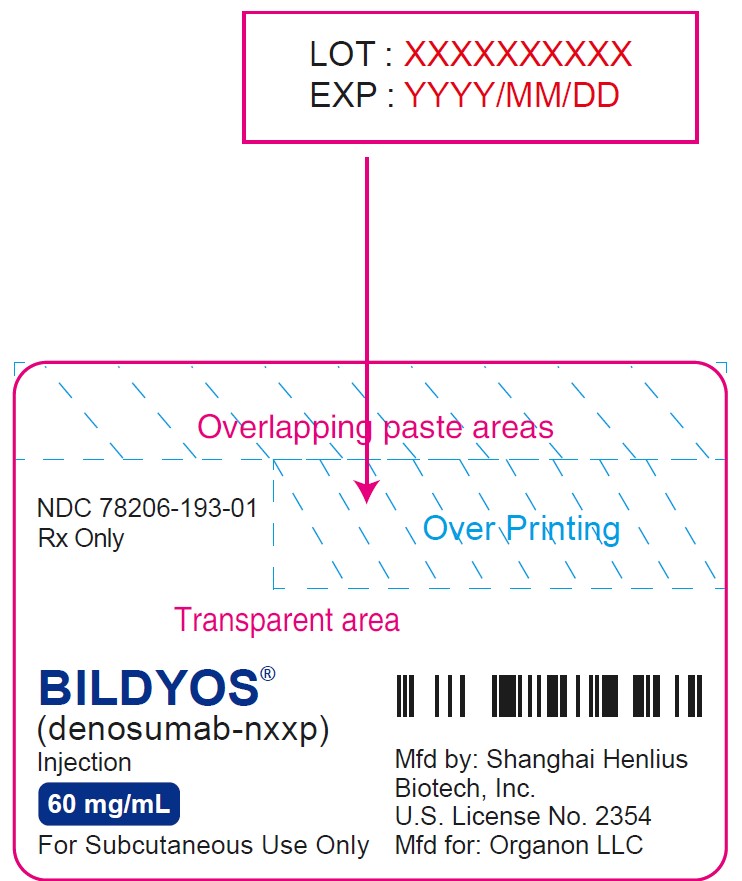 DRUG LABEL: BILDYOS
NDC: 78206-193 | Form: INJECTION, SOLUTION
Manufacturer: Organon LLC
Category: prescription | Type: HUMAN PRESCRIPTION DRUG LABEL
Date: 20250910

ACTIVE INGREDIENTS: DENOSUMAB 60 mg/1 mL
INACTIVE INGREDIENTS: ACETIC ACID 1.02 mg/1 mL; SORBITOL 47 mg/1 mL; POLYSORBATE 20 0.1 mg/1 mL; SODIUM HYDROXIDE

HIGHLIGHTS OF PRESCRIBING INFORMATION

These highlights do not include all the information needed to use BILDYOS safely and effectively. See full prescribing information for BILDYOS.
BILDYOS® (denosumab-nxxp) injection, for subcutaneous use
Initial U.S. Approval: 2025
BILDYOS® (denosumab-nxxp) is biosimilar [Biosimilar means that the biological product is approved based on data demonstrating that it is highly similar to an FDA-approved biological product, known as a reference product, and that there are no clinically meaningful differences between the biosimilar product and the reference product. Biosimilarity of BILDYOS has been demonstrated for the condition(s) of use (e.g., indication(s), dosing regimen(s), strength(s), dosage form(s) and route(s) of administration) described in its Full Prescribing Information.] to PROLIA®(denosumab)

WARNING: SEVERE HYPOCALCEMIA IN PATIENTS WITH ADVANCED KIDNEY DISEASE

See full prescribing information for complete boxed warning.

- Patients with advanced chronic kidney disease are at greater risk of severe hypocalcemia following denosumab products administration. Severe hypocalcemia resulting in hospitalization, life-threatening events and fatal cases have been reported. (5.1)
- The presence of chronic kidney disease-mineral bone disorder (CKD-MBD) markedly increases the risk of hypocalcemia. (5.1)
- Prior to initiating Bildyos in patients with advanced chronic kidney disease, evaluate for the presence of CKD-MBD. Treatment with Bildyos in these patients should be supervised by a healthcare provider with expertise in the diagnosis and management of CKD-MBD. (2.2, 5.1)

1 INDICATIONS AND USAGE

Bildyos is a RANK ligand (RANKL) inhibitor indicated for treatment:

- of postmenopausal women with osteoporosis at high risk for fracture. (1.1)
- to increase bone mass in men with osteoporosis at high risk for fracture. (1.2)
- of glucocorticoid-induced osteoporosis in men and women at high risk for fracture. (1.3)
- to increase bone mass in men at high risk for fracture receiving androgen deprivation therapy for nonmetastatic prostate cancer. (1.4)
- to increase bone mass in women at high risk for fracture receiving adjuvant aromatase inhibitor therapy for breast cancer. (1.5)

2 DOSAGE AND ADMINISTRATION

- Pregnancy must be ruled out prior to administration of Bildyos. (2.1)
- Before initiating Bildyos in patients with advanced chronic kidney disease, including dialysis patients, evaluate for the presence of chronic kidney disease mineral and bone disorder with intact parathyroid hormone, serum calcium, 25(OH) vitamin D, and 1,25 (OH)2vitamin D. (2.2, 5.1, 8.6)
- Bildyos should be administered by a healthcare provider. (2.3)
- Administer 60 mg every 6 months as a subcutaneous injection in the upper arm, upper thigh, or abdomen. (2.3)
- Instruct patients to take calcium 1000 mg daily and at least 400 IU vitamin D daily. (2.3)

3 DOSAGE FORMS AND STRENGTHS

Injection: 60 mg/mL solution in a single-dose prefilled syringe. (3)

4 CONTRAINDICATIONS

- Hypocalcemia. (4, 5.1)
- Pregnancy. (4, 8.1)
- Known hypersensitivity to denosumab products. (4, 5.3)

5 WARNINGS AND PRECAUTIONS

- Hypocalcemia: Pre-existing hypocalcemia must be corrected before initiating Bildyos. May worsen, especially in patients with renal impairment. Adequately supplement all patients with calcium and vitamin D. Concomitant use of calcimimetic drugs may also worsen hypocalcemia risk. Evaluate for presence of chronic kidney disease mineral-bone disorder. Monitor serum calcium. (5.1)
- Same Active Ingredient: Patients receiving Bildyos should not receive other denosumab products concomitantly. (5.2)
- Hypersensitivity including anaphylactic reactions may occur. Discontinue permanently if a clinically significant reaction occurs. (5.3)
- Osteonecrosis of the jaw: Has been reported with denosumab products. Monitor for symptoms. (5.4)
- Atypical femoral fractures: Have been reported. Evaluate patients with thigh or groin pain to rule out a femoral fracture. (5.5)
- Multiple vertebral fractures have been reported following treatment discontinuation. Patients should be transitioned to another antiresorptive agent if Bildyos is discontinued. (5.6)
- Serious infections including skin infections: May occur, including those leading to hospitalization. Advise patients to seek prompt medical attention if they develop signs or symptoms of infection, including cellulitis. (5.7)
- Dermatologic reactions: Dermatitis, rashes, and eczema have been reported. Consider discontinuing Bildyos if severe symptoms develop. (5.8)
- Severe bone, joint, muscle pain may occur. Discontinue use if severe symptoms develop. (5.9)
- Suppression of bone turnover: Significant suppression has been demonstrated. Monitor for consequences of bone over-suppression. (5.10)

6 ADVERSE REACTIONS

- Postmenopausal osteoporosis: Most common adverse reactions (> 5% and more common than placebo) were: back pain, pain in extremity, hypercholesterolemia, musculoskeletal pain, and cystitis. Pancreatitis has been reported in clinical trials. (6.1)
- Male osteoporosis: Most common adverse reactions (> 5% and more common than placebo) were: back pain, arthralgia, and nasopharyngitis.
- (6.1)
- Glucocorticoid-induced osteoporosis: Most common adverse reactions (> 3% and more common than active-control group) were: back pain, hypertension, bronchitis, and headache. (6.1)
- Bone loss due to hormone ablation for cancer: Most common adverse reactions (≥ 10% and more common than placebo) were: arthralgia and back pain. Pain in extremity and musculoskeletal pain have also been reported in clinical trials. (6.1)

To report SUSPECTED ADVERSE REACTIONS, contact Organon LLC, a subsidiary of Organon & Co., at 1-844-674-3200 or FDA at 1-800-FDA-1088 or www.fda.gov/medwatch.

8 USE IN SPECIFIC POPULATIONS

- Pregnant women and females of reproductive potential: Denosumab products may cause fetal harm when administered to pregnant women. Advise females of reproductive potential to use effective contraception during therapy, and for at least 5 months after the last dose of Bildyos. (8.1, 8.3)
- Pediatric patients: Bildyos is not approved for use in pediatric patients. (8.4)
- Renal impairment: No dose adjustment is necessary in patients with renal impairment. Patients with advanced chronic kidney disease (eGFR < 30 mL/min/1.73 m^2), including dialysis-dependent patients, are at greater risk of severe hypocalcemia. The presence of underlying chronic kidney disease-mineral bone disorder markedly increases the risk of hypocalcemia. (5.1, 8.6)

FULL PRESCRIBING INFORMATION

WARNING: SEVERE HYPOCALCEMIA IN PATIENTS WITH ADVANCED KIDNEY DISEASE

- Patients with advanced chronic kidney disease (eGFR < 30 mL/min/1.73 m^2), including dialysis dependent patients, are at greater risk of severe hypocalcemia following denosumab products administration. Severe hypocalcemia resulting in hospitalization, life-threatening events and fatal cases have been reported [see Warnings and Precautions (5.1)] .
- The presence of chronic kidney disease-mineral bone disorder (CKD-MBD) markedly increases the risk of hypocalcemia in these patients [see Warnings and Precautions (5.1)] .
- Prior to initiating Bildyos in patients with advanced chronic kidney disease, evaluate for the presence of CKD-MBD. Treatment with Bildyos in these patients should be supervised by a healthcare provider with expertise in the diagnosis and management of CKD-MBD [see Dosage and Administration (2.2) and Warnings and Precautions (5.1)].

1 INDICATIONS AND USAGE

1.1 Treatment of Postmenopausal Women with Osteoporosis at High Risk for Fracture

Bildyos is indicated for the treatment of postmenopausal women with osteoporosis at high risk for fracture, defined as a history of osteoporotic fracture, or multiple risk factors for fracture; or patients who have failed or are intolerant to other available osteoporosis therapy. In postmenopausal women with osteoporosis, denosumab reduces the incidence of vertebral, nonvertebral, and hip fractures [see Clinical Studies (14.1)] .

1.2 Treatment to Increase Bone Mass in Men with Osteoporosis

Bildyos is indicated for treatment to increase bone mass in men with osteoporosis at high risk for fracture, defined as a history of osteoporotic fracture, or multiple risk factors for fracture; or patients who have failed or are intolerant to other available osteoporosis therapy [see Clinical Studies (14.2)] .

1.3 Treatment of Glucocorticoid-Induced Osteoporosis

Bildyos is indicated for the treatment of glucocorticoid-induced osteoporosis in men and women at high risk of fracture who are either initiating or continuing systemic glucocorticoids in a daily dosage equivalent to 7.5 mg or greater of prednisone and expected to remain on glucocorticoids for at least 6 months. High risk of fracture is defined as a history of osteoporotic fracture, multiple risk factors for fracture, or patients who have failed or are intolerant to other available osteoporosis therapy [see Clinical Studies (14.3)] .

1.4 Treatment of Bone Loss in Men Receiving Androgen Deprivation Therapy for Prostate Cancer

Bildyos is indicated as a treatment to increase bone mass in men at high risk for fracture receiving androgen deprivation therapy (ADT) for nonmetastatic prostate cancer. In these patients denosumab also reduced the incidence of vertebral fractures [see Clinical Studies (14.4)] .

1.5 Treatment of Bone Loss in Women Receiving Adjuvant Aromatase Inhibitor Therapy for Breast Cancer

Bildyos is indicated as a treatment to increase bone mass in women at high risk for fracture receiving adjuvant aromatase inhibitor therapy for breast cancer [see Clinical Studies (14.5)] .

2 DOSAGE AND ADMINISTRATION

2.1 Pregnancy Testing Prior to Initiation of Bildyos

Pregnancy must be ruled out prior to administration of Bildyos. Perform pregnancy testing in all females of reproductive potential prior to administration of Bildyos. Based on findings in animals, denosumab products can cause fetal harm when administered to pregnant women [see Use in Specific Populations (8.1, 8.3)] .

2.2 Laboratory Testing in Patients with Advanced Chronic Kidney Disease Prior to Initiation of Bildyos

In patients with advanced chronic kidney disease [i.e., estimated glomerular filtration rate (eGFR) < 30 mL/min/1.73 m^2], including dialysis-dependent patients, evaluate for the presence of chronic kidney disease mineral and bone disorder (CKD-MBD) with intact parathyroid hormone (iPTH), serum calcium, 25(OH) vitamin D, and 1,25 (OH)2vitamin D prior to decisions regarding Bildyos treatment. Consider also assessing bone turnover status (serum markers of bone turnover or bone biopsy) to evaluate the underlying bone disease that may be present [see Warnings and Precautions (5.1)] .

2.3 Recommended Dosage

Bildyos should be administered by a healthcare provider.

The recommended dose of Bildyos is 60 mg administered as a single subcutaneous injection once every 6 months. Administer Bildyos via subcutaneous injection in the upper arm, the upper thigh, or the abdomen. All patients should receive calcium 1000 mg daily and at least 400 IU vitamin D daily [see Warnings and Precautions (5.1)] .

If a dose of Bildyos is missed, administer the injection as soon as the patient is available. Thereafter, schedule injections every 6 months from the date of the last injection.

2.4 Preparation and Administration

Parenteral drug products should be inspected visually for particulate matter and discoloration prior to administration whenever solution and container permit. Bildyos is clear to slightly opalescent, colorless to slightly yellow solution. Do not use if the solution is discolored or cloudy or if the solution contains visible particles or foreign particulate matter.

Prior to administration, Bildyos may be removed from the refrigerator and brought to room temperature up to 25°C (77°F) by standing in the original container. This generally takes 15 to 30 minutes. Do not warm Bildyos in any other way [see How Supplied/Storage and Handling (16)].

Instructions for Administration of Bildyos Prefilled Syringe with Needle Safety Guard

• Bildyos single-dose prefilled syringe contains a safety guard that activates to cover the needle after the injection is finished. The safety guard helps to prevent needlesticks.

Step 1: Remove Needle Cap
Carefully pull the black needle cap straight out and away from your body.

Step 2: Administer Subcutaneous Injection

Choose an injection site. The recommended injection sites for Bildyos include the upper arm, OR the upper thigh, OR the abdomen.

Pinch your injection site to create a firm surface. Hold the pinch. Insert the needle into the skin at 45 to 90 degrees.

Push the plunger with slow and constant pressure until you feel or hear a “snap”. Push all the way down through the snap.

Release your thumb. Then lift the syringe off skin. After releasing the plunger, the pre-filled syringe safety guard will safely cover the injection needle.

Immediately dispose of the syringe and needle cap in the nearest sharps container. Do not put the needle cap back on the used syringe.

3 DOSAGE FORMS AND STRENGTHS

- Injection: 60 mg/mL clear to slightly opalescent, colorless to slightly yellow solution in a single-dose prefilled syringe.

4 CONTRAINDICATIONS

Bildyos is contraindicated in:

- Patients with hypocalcemia: Pre-existing hypocalcemia must be corrected prior to initiating therapy with Bildyos [see Warnings and Precautions (5.1)] .
- Pregnant women: Denosumab products may cause fetal harm when administered to a pregnant woman. In women of reproductive potential, pregnancy testing should be performed prior to initiating treatment with Bildyos [see Use in Specific Populations (8.1)] .
- Patients with hypersensitivity to denosumab products: Bildyos is contraindicated in patients with a history of systemic hypersensitivity to any component of the product. Reactions have included anaphylaxis, facial swelling, and urticaria [see Warnings and Precautions (5.3), Adverse Reactions (6.2)] .

5 WARNINGS AND PRECAUTIONS

5.1 Severe Hypocalcemia and Mineral Metabolism Changes

Denosumab products can cause severe hypocalcemia and fatal cases have been reported. Pre-existing hypocalcemia must be corrected prior to initiating therapy with Bildyos. Adequately supplement all patients with calcium and vitamin D [see Dosage and Administration (2.1), Contraindications (4), and Adverse Reactions (6.1)].

In patients without advanced chronic kidney disease who are predisposed to hypocalcemia and disturbances of mineral metabolism (e.g., history of hypoparathyroidism, thyroid surgery, parathyroid surgery, malabsorption syndromes, excision of small intestine, treatment with other calcium-lowering drugs), assess serum calcium and mineral levels (phosphorus and magnesium) 10 to 14 days after Bildyos injection. In some postmarketing cases, hypocalcemia persisted for weeks or months and required frequent monitoring and intravenous and/or oral calcium replacement, with or without vitamin D.

Patients with Advanced Chronic Kidney Disease

Patients with advanced chronic kidney disease [i.e., eGFR < 30 mL/min/1.73 m^2] including dialysis-dependent patients are at greater risk for severe hypocalcemia following denosumab products administration. Severe hypocalcemia resulting in hospitalization, life-threatening events and fatal cases have been reported. The presence of underlying chronic kidney disease-mineral bone disorder (CKD-MBD, renal osteodystrophy) markedly increases the risk of hypocalcemia. Concomitant use of calcimimetic drugs may also worsen hypocalcemia risk.

To minimize the risk of hypocalcemia in patients with advanced chronic kidney disease, evaluate for the presence of chronic kidney disease, mineral and bone disorder with intact parathyroid hormone (iPTH), serum calcium, 25(OH) vitamin D, and 1,25 (OH)2vitamin D prior to decisions regarding Bildyos treatment. Consider also assessing bone turnover status (serum markers of bone turnover or bone biopsy) to evaluate the underlying bone disease that may be present. Monitor serum calcium weekly for the first month after Bildyos administration and monthly thereafter. Instruct all patients with advanced chronic kidney disease, including those who are dialysis-dependent, about the symptoms of hypocalcemia and the importance of maintaining serum calcium levels with adequate calcium and activated vitamin D supplementation. Treatment with Bildyos in these patients should be supervised by a healthcare provider who is experienced in diagnosis and management of CKD-MBD.

5.2 Drug Products with Same Active Ingredient

Patients receiving Bildyos should not receive other denosumab products concomitantly.

5.3 Hypersensitivity

Clinically significant hypersensitivity including anaphylaxis has been reported with denosumab products. Symptoms have included hypotension, dyspnea, throat tightness, facial and upper airway edema, pruritus, and urticaria. If an anaphylactic or other clinically significant allergic reaction occurs, initiate appropriate therapy, and discontinue further use of Bildyos [see Contraindications (4), Adverse Reactions (6.2)] .

5.4 Osteonecrosis of the Jaw

Osteonecrosis of the jaw (ONJ), which can occur spontaneously, is generally associated with tooth extraction and/or local infection with delayed healing. ONJ has been reported in patients receiving denosumab products [see Adverse Reactions (6.1)]. A routine oral exam should be performed by the prescriber prior to initiation of Bildyos treatment. A dental examination with appropriate preventive dentistry is recommended prior to treatment with Bildyos in patients with risk factors for ONJ such as invasive dental procedures (e.g. tooth extraction, dental implants, oral surgery), diagnosis of cancer, concomitant therapies (e.g. chemotherapy, corticosteroids, angiogenesis inhibitors), poor oral hygiene, and comorbid disorders (e.g. periodontal and/or other pre-existing dental disease, anemia, coagulopathy, infection, ill-fitting dentures). Good oral hygiene practices should be maintained during treatment with Bildyos. Concomitant administration of drugs associated with ONJ may increase the risk of developing ONJ. The risk of ONJ may increase with duration of exposure to denosumab products.

For patients requiring invasive dental procedures, clinical judgment of the treating physician and/or oral surgeon should guide the management plan of each patient based on individual benefit-risk assessment.

Patients who are suspected of having or who develop ONJ while on Bildyos should receive care by a dentist or an oral surgeon. In these patients, extensive dental surgery to treat ONJ may exacerbate the condition. Discontinuation of Bildyos therapy should be considered based on individual benefit-risk assessment.

5.5 Atypical Subtrochanteric and Diaphyseal Femoral Fractures

Atypical low energy or low trauma fractures of the shaft have been reported in patients receiving denosumab products [see Adverse Reactions (6.1)] . These fractures can occur anywhere in the femoral shaft from just below the lesser trochanter to above the supracondylar flare and are transverse or short oblique in orientation without evidence of comminution. Causality has not been established as these fractures also occur in osteoporotic patients who have not been treated with antiresorptive agents.

Atypical femoral fractures most commonly occur with minimal or no trauma to the affected area. They may be bilateral, and many patients report prodromal pain in the affected area, usually presenting as dull, aching thigh pain, weeks to months before a complete fracture occurs. A number of reports note that patients were also receiving treatment with glucocorticoids (e.g. prednisone) at the time of fracture.

During Bildyos treatment, patients should be advised to report new or unusual thigh, hip, or groin pain. Any patient who presents with thigh or groin pain should be suspected of having an atypical fracture and should be evaluated to rule out an incomplete femur fracture. Patient presenting with an atypical femur fracture should also be assessed for symptoms and signs of fracture in the contralateral limb. Interruption of Bildyos therapy should be considered, pending a benefit-risk assessment, on an individual basis.

5.6 Multiple Vertebral Fractures (MVF) Following Discontinuation of Treatment

Following discontinuation of denosumab treatment, fracture risk increases, including the risk of multiple vertebral fractures. Treatment with denosumab results in significant suppression of bone turnover and cessation of denosumab treatment results in increased bone turnover above pretreatment values 9 months after the last dose of denosumab. Bone turnover then returns to pretreatment values 24 months after the last dose of denosumab. In addition, bone mineral density (BMD) returns to pretreatment values within 18 months after the last injection [see Clinical Pharmacology (12.2), Clinical Studies (14.1)].

New vertebral fractures occurred as early as 7 months (on average 19 months) after the last dose of denosumab. Prior vertebral fracture was a predictor of multiple vertebral fractures after denosumab discontinuation. Evaluate an individual's benefit-risk before initiating treatment with Bildyos.

If Bildyos treatment is discontinued, patients should be transitioned to an alternative antiresorptive therapy [see Adverse Reactions (6.1)] .

5.7 Serious Infections

In a clinical trial of over 7800 women with postmenopausal osteoporosis, serious infections leading to hospitalization were reported more frequently in the denosumab group than in the placebo group [see Adverse Reactions (6.1)] . Serious skin infections, as well as infections of the abdomen, urinary tract, and ear, were more frequent in patients treated with denosumab. Endocarditis was also reported more frequently in denosumab treated patients. The incidence of opportunistic infections was similar between placebo and denosumab groups, and the overall incidence of infections was similar between the treatment groups. Advise patients to seek prompt medical attention if they develop signs or symptoms of severe infection, including cellulitis.

Patients on concomitant immunosuppressant agents or with impaired immune systems may be at increased risk for serious infections. Consider the benefit-risk profile in such patients before treating with Bildyos. In patients who develop serious infections while on Bildyos, prescribers should assess the need for continued Bildyos therapy.

5.8 Dermatologic Adverse Reactions

In a large clinical trial of over 7800 women with postmenopausal osteoporosis, epidermal and dermal adverse events such as dermatitis, eczema, and rashes occurred at a significantly higher rate in the denosumab group compared to the placebo group. Most of these events were not specific to the injection site [see Adverse Reactions (6.1)] . Consider discontinuing Bildyos if severe symptoms develop.

5.9 Musculoskeletal Pain

In postmarketing experience, severe and occasionally incapacitating bone, joint, and/or muscle pain has been reported in patients taking denosumab products [see Adverse Reactions (6.2)] . The time to onset of symptoms varied from one day to several months after starting denosumab products. Consider discontinuing use if severe symptoms develop [see Patient Counseling Information (17)] .

5.10 Suppression of Bone Turnover

In clinical trials in women with postmenopausal osteoporosis, treatment with denosumab resulted in significant suppression of bone remodeling as evidenced by markers of bone turnover and bone histomorphometry [see Clinical Pharmacology (12.2), Clinical Studies (14.1)] . The significance of these findings and the effect of long-term treatment with denosumab products are unknown. The long-term consequences of the degree of suppression of bone remodeling observed with denosumab may contribute to adverse outcomes such as osteonecrosis of the jaw, atypical fractures, and delayed fracture healing. Monitor patients for these consequences.

5.11 Hypercalcemia in Pediatric Patients with Osteogenesis Imperfecta

Bildyos is not approved for use in pediatric patients. Hypercalcemia has been reported in pediatric patients with osteogenesis imperfecta treated with denosumab products. Some cases required hospitalization [see Use in Specific Populations (8.4)] .

6 ADVERSE REACTIONS

The following serious adverse reactions are discussed below and also elsewhere in the labeling:

- Severe Hypocalcemia and Mineral Metabolism Changes [see Warnings and Precautions (5.1)]
- Hypersensitivity [see Warnings and Precautions (5.3) ]
- Osteonecrosis of the Jaw [see Warnings and Precautions (5.4)]
- Atypical Subtrochanteric and Diaphyseal Femoral Fractures [see Warnings and Precautions (5.5)]
- Multiple Vertebral Fractures (MVF) Following Treatment Discontinuation [see Warnings and Precautions (5.6)]
- Serious Infections [see Warnings and Precautions (5.7)]
- Dermatologic Adverse Reactions [see Warnings and Precautions (5.8)]

The most common adverse reactions reported with denosumab products in patients with postmenopausal osteoporosis are back pain, pain in extremity, musculoskeletal pain, hypercholesterolemia, and cystitis.

The most common adverse reactions reported with denosumab products in men with osteoporosis are back pain, arthralgia, and nasopharyngitis.

The most common adverse reactions reported with denosumab products in patients with glucocorticoid-induced osteoporosis are back pain, hypertension, bronchitis, and headache.

The most common (per patient incidence ≥ 10%) adverse reactions reported with denosumab products in patients with bone loss receiving androgen deprivation therapy for prostate cancer or adjuvant aromatase inhibitor therapy for breast cancer are arthralgia and back pain. Pain in extremity and musculoskeletal pain have also been reported in clinical trials.

The most common adverse reactions leading to discontinuation of denosumab products in patients with postmenopausal osteoporosis are back pain and constipation.

6.1 Clinical Trials Experience

Because clinical studies are conducted under widely varying conditions, adverse reaction rates observed in the clinical studies of a drug cannot be directly compared to rates in the clinical studies of another drug and may not reflect the rates observed in clinical practice.

Treatment of Postmenopausal Women with Osteoporosis

The safety of denosumab in the treatment of postmenopausal osteoporosis was assessed in a 3-year, randomized, double-blind, placebo-controlled, multinational study of 7808 postmenopausal women aged 60 to 91 years. A total of 3876 women were exposed to placebo and 3886 women were exposed to denosumab administered subcutaneously once every 6 months as a single 60 mg dose. All women were instructed to take at least 1000 mg of calcium and 400 IU of vitamin D supplementation per day.

The incidence of all-cause mortality was 2.3% (n = 90) in the placebo group and 1.8% (n = 70) in the denosumab group. The incidence of nonfatal serious adverse events was 24.2% in the placebo group and 25.0% in the denosumab group. The percentage of patients who withdrew from the study due to adverse events was 2.1% and 2.4% for the placebo and denosumab groups, respectively. The most common adverse reactions reported with denosumab in patients with postmenopausal osteoporosis are back pain, pain in extremity, musculoskeletal pain, hypercholesterolemia, and cystitis.

Adverse reactions reported in ≥ 2% of postmenopausal women with osteoporosis and more frequently in the denosumab-treated women than in the placebo-treated women are shown in the table below.

Table 1. Adverse Reactions Occurring in ≥ 2% of Patients with Osteoporosis and More Frequently than in Placebo-treated Patients
Preferred Term | Denosumab (N = 3886) n (%) | Placebo (N = 3876) n (%)
Back pain Pain in extremity Musculoskeletal pain Hypercholesterolemia Cystitis Vertigo Upper respiratory tract infection Edema peripheral Sciatica Bone pain Abdominal pain upper Anemia Insomnia Myalgia Angina pectoris Rash Pharyngitis Asthenia Pruritus Flatulence Spinal osteoarthritis Gastroesophageal reflux disease Herpes zoster | 1347 (34.7) 453 (11.7) 297 (7.6) 280 (7.2) 228 (5.9) 195 (5.0) 190 (4.9) 189 (4.9) 178 (4.6) 142 (3.7) 129 (3.3) 129 (3.3) 126 (3.2) 114 (2.9) 101 (2.6) 96 (2.5) 91 (2.3) 90 (2.3) 87 (2.2) 84 (2.2) 82 (2.1) 80 (2.1) 79 (2.0) | 1340 (34.6) 430 (11.1) 291 (7.5) 236 (6.1) 225 (5.8) 187 (4.8) 167 (4.3) 155 (4.0) 149 (3.8) 117 (3.0) 111 (2.9) 107 (2.8) 122 (3.1) 94 (2.4) 87 (2.2) 79 (2.0) 78 (2.0) 73 (1.9) 82 (2.1) 53 (1.4) 64 (1.7) 66 (1.7) 72 (1.9)

Hypocalcemia

Decreases in serum calcium levels to less than 8.5 mg/dL at any visit were reported in 0.4% women in the placebo group and 1.7% women in the denosumab group. The nadir in serum calcium level occurred at approximately day 10 after denosumab dosing in subjects with normal renal function.

In clinical studies, subjects with impaired renal function were more likely to have greater reductions in serum calcium levels compared to subjects with normal renal function. In a study of 55 subjects with varying degrees of renal function, serum calcium levels < 7.5 mg/dL or symptomatic hypocalcemia were observed in 5 subjects. These included no subjects in the normal renal function group, 10% of subjects in the creatinine clearance 50 to 80 mL/min group, 29% of subjects in the creatinine clearance < 30 mL/min group, and 29% of subjects in the hemodialysis group. These subjects did not receive calcium and vitamin D supplementation. In a study of 4550 postmenopausal women with osteoporosis, the mean change from baseline in serum calcium level 10 days after denosumab dosing was -5.5% in subjects with creatinine clearance < 30 mL/min vs. -3.1% in subjects with creatinine clearance ≥ 30 mL/min.

Serious Infections

Receptor activator of nuclear factor kappa-B ligand (RANKL) is expressed on activated T and B lymphocytes and in lymph nodes. Therefore, a RANKL inhibitor such as denosumab products may increase the risk of infection.

In the clinical study of 7808 postmenopausal women with osteoporosis, the incidence of infections resulting in death was 0.2% in both placebo and denosumab treatment groups. However, the incidence of nonfatal serious infections was 3.3% in the placebo and 4.0% in the denosumab groups. Hospitalizations due to serious infections in the abdomen (0.7% placebo vs. 0.9% denosumab), urinary tract (0.5% placebo vs. 0.7% denosumab), and ear (0.0% placebo vs. 0.1% denosumab) were reported. Endocarditis was reported in no placebo patients and 3 patients receiving denosumab.

Skin infections, including erysipelas and cellulitis, leading to hospitalization were reported more frequently in patients treated with denosumab (< 0.1% placebo vs. 0.4% denosumab).

The incidence of opportunistic infections was similar to that reported with placebo.

Dermatologic Adverse Reactions

A significantly higher number of patients treated with denosumab developed epidermal and dermal adverse events (such as dermatitis, eczema, and rashes), with these events reported in 8.2% of the placebo and 10.8% of the denosumab groups (p < 0.0001). Most of these events were not specific to the injection site [see Warnings and Precautions (5.8)].

Osteonecrosis of the Jaw

ONJ has been reported in the osteoporosis clinical trial program in patients treated with denosumab [see Warnings and Precautions (5.4)].

Atypical Subtrochanteric and Diaphyseal Femoral Fractures

In the osteoporosis clinical trial program, atypical femoral fractures were reported in patients treated with denosumab. The duration of denosumab exposure to time of atypical femoral fracture diagnosis was as early as 2½ years [see Warnings and Precautions (5.5)] .

Multiple Vertebral Fractures (MVF) Following Treatment Discontinuation

In the osteoporosis clinical trial program, multiple vertebral fractures were reported in patients after discontinuation of denosumab. In the phase 3 trial in women with postmenopausal osteoporosis, 6% of women who discontinued denosumab and remained in the study developed new vertebral fractures, and 3% of women who discontinued denosumab and remained in the study developed multiple new vertebral fractures. The mean time to onset of multiple vertebral fractures was 17 months (range: 7-43 months) after the last injection of denosumab. Prior vertebral fracture was a predictor of multiple vertebral fractures after discontinuation [see Warnings and Precautions (5.6)] .

Pancreatitis

Pancreatitis was reported in 4 patients (0.1%) in the placebo and 8 patients (0.2%) in the denosumab groups. Of these reports, 1 patient in the placebo group and all 8 patients in the denosumab group had serious events, including one death in the denosumab group. Several patients had a prior history of pancreatitis. The time from product administration to event occurrence was variable.

New Malignancies

The overall incidence of new malignancies was 4.3% in the placebo and 4.8% in the denosumab groups. New malignancies related to the breast (0.7% placebo vs. 0.9% denosumab), reproductive system (0.2% placebo vs. 0.5% denosumab), and gastrointestinal system (0.6% placebo vs. 0.9% denosumab) were reported. A causal relationship to drug exposure has not been established.

Treatment to Increase Bone Mass in Men with Osteoporosis

The safety of denosumab in the treatment of men with osteoporosis was assessed in a 1-year randomized, double-blind, placebo-controlled study. A total of 120 men were exposed to placebo and 120 men were exposed to denosumab administered subcutaneously once every 6 months as a single 60 mg dose. All men were instructed to take at least 1000 mg of calcium and 800 IU of vitamin D supplementation per day.

The incidence of all-cause mortality was 0.8% (n = 1) in the placebo group and 0.8% (n = 1) in the denosumab group. The incidence of nonfatal serious adverse events was 7.5% in the placebo group and 8.3% in the denosumab group. The percentage of patients who withdrew from the study due to adverse events was 0% and 2.5% for the placebo and denosumab groups, respectively.

Adverse reactions reported in ≥ 5% of men with osteoporosis and more frequently with denosumab than in the placebo-treated patients were: back pain (6.7% placebo vs. 8.3% denosumab), arthralgia (5.8% placebo vs. 6.7% denosumab), and nasopharyngitis (5.8% placebo vs. 6.7% denosumab).

Serious Infections

Serious infection was reported in 1 patient (0.8%) in the placebo group and no patients in the denosumab group.

Dermatologic Adverse Reactions

Epidermal and dermal adverse events (such as dermatitis, eczema, and rashes) were reported in 4 patients (3.3%) in the placebo group and 5 patients (4.2%) in the denosumab group.

Osteonecrosis of the Jaw

No cases of ONJ were reported.

Pancreatitis

Pancreatitis was reported in 1 patient (0.8%) in the placebo group and 1 patient (0.8%) in the denosumab group.

New Malignancies

New malignancies were reported in no patients in the placebo group and 4 (3.3%) patients (3 prostate cancers, 1 basal cell carcinoma) in the denosumab group.

Treatment of Glucocorticoid-Induced Osteoporosis

The safety of denosumab in the treatment of glucocorticoid-induced osteoporosis was assessed in the 1-year, primary analysis of a 2-year randomized, multi-center, double-blind, parallel-group, active-controlled study of 795 patients (30% men and 70% women) aged 20 to 94 (mean age of 63 years) treated with greater than or equal to 7.5 mg/day oral prednisone (or equivalent). A total of 384 patients were exposed to 5 mg oral daily bisphosphonate (active-control) and 394 patients were exposed to denosumab administered once every 6 months as a 60 mg subcutaneous dose. All patients were instructed to take at least 1000 mg of calcium and 800 IU of vitamin D supplementation per day.

The incidence of all-cause mortality was 0.5% (n = 2) in the active-control group and 1.5% (n = 6) in the denosumab group. The incidence of serious adverse events was 17% in the active-control group and 16% in the denosumab group. The percentage of patients who withdrew from the study due to adverse events was 3.6% and 3.8% for the active-control and denosumab groups, respectively.

Adverse reactions reported in ≥ 2% of patients with glucocorticoid-induced osteoporosis and more frequently with denosumab than in the active-control-treated patients are shown in the table below.

Table 2. Adverse Reactions Occurring in ≥ 2% of Patients with Glucocorticoid-induced Osteoporosis and More Frequently with Denosumab than in Active-Control-treated Patients
Preferred Term | Denosumab (N=394) n (%) | Oral Daily Bisphosphonate (Active-Control) (N=384) n (%)
Back pain | 18 (4.6) | 17 (4.4)
Hypertension | 15 (3.8) | 13 (3.4)
Bronchitis | 15 (3.8) | 11 (2.9)
Headache | 14 (3.6) | 7 (1.8)
Dyspepsia | 12 (3.0) | 10 (2.6)
Urinary tract infection | 12 (3.0) | 8 (2.1)
Abdominal pain upper | 12 (3.0) | 7 (1.8)
Upper respiratory tract infection | 11 (2.8) | 10 (2.6)
Constipation | 11 (2.8) | 6 (1.6)
Vomiting | 10 (2.5) | 6 (1.6)
Dizziness | 9 (2.3) | 8 (2.1)
Fall | 8 (2.0) | 7 (1.8)
Polymyalgia rheumatica* | 8 (2.0) | 1 (0.3)
* Events of worsening of underlying polymyalgia rheumatica.

Osteonecrosis of the Jaw

No cases of ONJ were reported.

Atypical Subtrochanteric and Diaphyseal Femoral Fractures

Atypical femoral fractures were reported in 1 patient treated with denosumab. The duration of denosumab exposure to time of atypical femoral fracture diagnosis was at 8.0 months [see Warnings and Precautions (5.5)] .

Serious Infections

Serious infection was reported in 15 patients (3.9%) in the active-control group and 17 patients (4.3%) in the denosumab group.

Dermatologic Adverse Reactions

Epidermal and dermal adverse events (such as dermatitis, eczema, and rashes) were reported in 16 patients (4.2%) in the active-control group and 15 patients (3.8%) in the denosumab group.

Treatment of Bone Loss in Patients Receiving Androgen Deprivation Therapy for Prostate Cancer or Adjuvant Aromatase Inhibitor Therapy for Breast Cancer

The safety of denosumab in the treatment of bone loss in men with nonmetastatic prostate cancer receiving androgen deprivation therapy (ADT) was assessed in a 3-year, randomized, double-blind, placebo-controlled, multinational study of 1468 men aged 48 to 97 years. A total of 725 men were exposed to placebo and 731 men were exposed to denosumab administered once every 6 months as a single 60 mg subcutaneous dose. All men were instructed to take at least 1000 mg of calcium and 400 IU of vitamin D supplementation per day.

The incidence of serious adverse events was 30.6% in the placebo group and 34.6% in the denosumab group. The percentage of patients who withdrew from the study due to adverse events was 6.1% and 7.0% for the placebo and denosumab groups, respectively.

The safety of denosumab in the treatment of bone loss in women with nonmetastatic breast cancer receiving aromatase inhibitor (AI) therapy was assessed in a 2-year, randomized, double-blind, placebo-controlled, multinational study of 252 postmenopausal women aged 35 to 84 years. A total of 120 women were exposed to placebo and 129 women were exposed to denosumab administered once every 6 months as a single 60 mg subcutaneous dose. All women were instructed to take at least 1000 mg of calcium and 400 IU of vitamin D supplementation per day.

The incidence of serious adverse events was 9.2% in the placebo group and 14.7% in the denosumab group. The percentage of patients who withdrew from the study due to adverse events was 4.2% and 0.8% for the placebo and denosumab groups, respectively.

Adverse reactions reported in ≥ 10% of denosumab-treated patients receiving ADT for prostate cancer or adjuvant AI therapy for breast cancer, and more frequently than in the placebo-treated patients were: arthralgia (13.0% placebo vs. 14.3% denosumab) and back pain (10.5% placebo vs. 11.5% denosumab). Pain in extremity (7.7% placebo vs. 9.9% denosumab) and musculoskeletal pain (3.8% placebo vs. 6.0% denosumab) have also been reported in clinical trials. Additionally, in denosumab-treated men with nonmetastatic prostate cancer receiving ADT, a greater incidence of cataracts was observed (1.2% placebo vs. 4.7% denosumab). Hypocalcemia (serum calcium < 8.4 mg/dL) was reported only in denosumab-treated patients (2.4% vs. 0.0%) at the month 1 visit.

6.2 Postmarketing Experience

Because postmarketing reactions are reported voluntarily from a population of uncertain size, it is not always possible to reliably estimate their frequency or establish a causal relationship to drug exposure.

The following adverse reactions have been identified during post-approval use of denosumab products:

- Drug-related hypersensitivity reactions: anaphylaxis, rash, urticaria, facial swelling, and erythema.
- Hypocalcemia: severe symptomatic hypocalcemia resulting in hospitalization, life-threatening events and fatal cases.
- Musculoskeletal pain, including severe cases.
- Parathyroid hormone (PTH): Marked elevation in serum PTH in patients with severe renal impairment (creatinine clearance < 30 mL/min) or receiving dialysis.
- Multiple vertebral fractures following treatment discontinuation.
- Cutaneous and mucosal lichenoid drug eruptions (e.g., lichen planus-like reactions).
- Alopecia.
- Vasculitis (e.g., ANCA positive vasculitis, leukocytoclastic vasculitis).
- Drug reaction with eosinophilia and systemic symptoms (DRESS) syndrome.

8 USE IN SPECIFIC POPULATIONS

8.1 Pregnancy

Risk Summary

Bildyos is contraindicated for use in pregnant women because it may cause harm to a fetus. There are insufficient data with denosumab products use in pregnant women to inform any drug-associated risks for adverse developmental outcomes. In uterodenosumab exposure from cynomolgus monkeys dosed monthly with denosumab throughout pregnancy at a dose 50-fold higher than the recommended human dose based on body weight resulted in increased fetal loss, stillbirths, and postnatal mortality, and absent lymph nodes, abnormal bone growth, and decreased neonatal growth [see Data] .

Data

Animal Data

The effects of denosumab on prenatal development have been studied in both cynomolgus monkeys and genetically engineered mice in which RANK ligand (RANKL) expression was turned off by gene removal (a “knockout mouse”). In cynomolgus monkeys dosed subcutaneously with denosumab throughout pregnancy starting at gestational day 20 and at a pharmacologically active dose 50-fold higher than the recommended human dose based on body weight, there was increased fetal loss during gestation, stillbirths, and postnatal mortality. Other findings in offspring included absence of axillary, inguinal, mandibular, and mesenteric lymph nodes; abnormal bone growth, reduced bone strength, reduced hematopoiesis, dental dysplasia, and tooth malalignment; and decreased neonatal growth. At birth out to 1 month of age, infants had measurable blood levels of denosumab (22-621% of maternal levels).

Following a recovery period from birth out to 6 months of age, the effects on bone quality and strength returned to normal; there were no adverse effects on tooth eruption, though dental dysplasia was still apparent; axillary and inguinal lymph nodes remained absent, while mandibular and mesenteric lymph nodes were present, though small; and minimal to moderate mineralization in multiple tissues was seen in one recovery animal. There was no evidence of maternal harm prior to labor; adverse maternal effects occurred infrequently during labor. Maternal mammary gland development was normal. There was no fetal NOAEL (no observable adverse effect level) established for this study because only one dose of 50 mg/kg was evaluated. Mammary gland histopathology at 6 months of age was normal in female offspring exposed to denosumab in utero; however, development and lactation have not been fully evaluated.

In RANKL knockout mice, absence of RANKL (the target of denosumab) also caused fetal lymph node agenesis and led to postnatal impairment of dentition and bone growth. Pregnant RANKL knockout mice showed altered maturation of the maternal mammary gland, leading to impaired lactation [see Use in Specific Populations (8.2), Nonclinical Toxicology (13.2)] .

The no effect dose for denosumab product-induced teratogenicity is unknown. However, a Cmaxof 22.9 ng/mL was identified in cynomolgus monkeys as a level in which no biologic effects (NOEL) of denosumab were observed (no inhibition of RANKL) [see Clinical Pharmacology (12.3)].

8.2 Lactation

Risk Summary

There is no information regarding the presence of denosumab products in human milk, the effects on the breastfed infant, or the effects on milk production. Denosumab was detected in the maternal milk of cynomolgus monkeys up to 1 month after the last dose of denosumab (≤ 0.5% milk:serum ratio) and maternal mammary gland development was normal, with no impaired lactation. However, pregnant RANKL knockout mice showed altered maturation of the maternal mammary gland, leading to impaired lactation [see Use in Specific Populations (8.1), Nonclinical Toxicology (13.2)] .

8.3 Females and Males of Reproductive Potential

Based on findings in animals, denosumab products can cause fetal harm when administered to a pregnant woman [see Use in Specific Populations (8.1)] .

Pregnancy Testing

Verify the pregnancy status of females of reproductive potential prior to initiating Bildyos treatment.

Contraception

Females

Advise females of reproductive potential to use effective contraception during therapy, and for at least 5 months after the last dose of Bildyos.

Males

Denosumab was present at low concentrations (approximately 2% of serum exposure) in the seminal fluid of male subjects given denosumab. Following vaginal intercourse, the maximum amount of denosumab delivered to a female partner would result in exposures approximately 11000 times lower than the prescribed 60 mg subcutaneous dose, and at least 38 times lower than the NOEL in monkeys.

Therefore, male condom use would not be necessary as it is unlikely that a female partner or fetus would be exposed to pharmacologically relevant concentrations of denosumab products via seminal fluid [see Clinical Pharmacology (12.3)] .

8.4 Pediatric Use

The safety and effectiveness of Bildyos have not been established in pediatric patients.

In one multicenter, open-label study with denosumab conducted in 153 pediatric patients with osteogenesis imperfecta, aged 2 to 17 years, evaluating fracture risk reduction, efficacy was not demonstrated.

Hypercalcemia has been reported in pediatric patients with osteogenesis imperfecta treated with denosumab products. Some cases required hospitalization and were complicated by acute renal injury [see Warnings and Precautions (5.11)] . Clinical studies in pediatric patients with osteogenesis imperfecta were terminated early due to the occurrence of life-threatening events and hospitalizations due to hypercalcemia.

Safety and effectiveness were not demonstrated for the treatment of glucocorticoid-induced osteoporosis in one multicenter, randomized, double-blind, placebo-controlled, parallel-group study conducted in 24 pediatric patients with glucocorticoid-induced osteoporosis, aged 5 to 17 years, evaluating change from baseline in lumbar spine BMD Z-score.

Based on results from animal studies, denosumab may negatively affect long-bone growth and dentition in pediatric patients below the age of 4 years.

Juvenile Animal Toxicity Data

Treatment with denosumab products may impair long-bone growth in children with open growth plates and may inhibit eruption of dentition. In neonatal rats, inhibition of RANKL (the target of denosumab therapy) with a construct of osteoprotegerin bound to Fc (OPG-Fc) at doses ≤ 10 mg/kg was associated with inhibition of bone growth and tooth eruption. Adolescent primates treated with denosumab at doses 10 and 50 times (10 and 50 mg/kg dose) higher than the recommended human dose of 60 mg administered every 6 months, based on body weight (mg/kg), had abnormal growth plates, considered to be consistent with the pharmacological activity of denosumab [see Nonclinical Toxicology (13.2)] .

Cynomolgus monkeys exposed in utero to denosumab exhibited bone abnormalities, an absence of axillary, inguinal, mandibular, and mesenteric lymph nodes, reduced hematopoiesis, tooth malalignment, and decreased neonatal growth. Some bone abnormalities recovered once exposure was ceased following birth; however, axillary, and inguinal lymph nodes remained absent 6 months post-birth [see Use in Specific Populations (8.1)] .

8.5 Geriatric Use

Of the total number of patients in clinical studies of denosumab, 9943 patients (76%) were ≥ 65 years old, while 3576 (27%) were ≥ 75 years old. Of the patients in the osteoporosis study in men, 133 patients (55%) were ≥ 65 years old, while 39 patients (16%) were ≥ 75 years old. Of the patients in the glucocorticoid-induced osteoporosis study, 355 patients (47%) were ≥ 65 years old, while 132 patients (17%) were ≥ 75 years old. No overall differences in safety or efficacy were observed between these patients and younger patients, and other reported clinical experience has not identified differences in responses between the elderly and younger patients, but greater sensitivity of some older individuals cannot be ruled out.

8.6 Renal Impairment

No dose adjustment is necessary in patients with renal impairment.

Severe hypocalcemia resulting in hospitalization, life-threatening events and fatal cases have been reported postmarketing. In clinical studies, patients with advanced chronic kidney disease (i.e., eGFR < 30 mL/min/1.73 m^2), including dialysis-dependent patients, were at greater risk of developing hypocalcemia. The presence of underlying chronic kidney disease-mineral bone disorder (CKD-MBD, renal osteodystrophy) markedly increases the risk of hypocalcemia. Concomitant use of calcimimetic drugs may also worsen hypocalcemia risk. Consider the benefits and risks to the patient when administering Bildyos to patients with advanced chronic kidney disease. Monitor calcium and mineral levels (phosphorus and magnesium). Adequate intake of calcium and vitamin D is important in patients with advanced chronic kidney disease including dialysis-dependent patients [see Dosage and Administration (2.2), Warnings and Precautions (5.1), Adverse Reactions (6.1) and Clinical Pharmacology (12.3)] .

11 DESCRIPTION

Denosumab-nxxp is a human IgG2 monoclonal antibody with affinity and specificity for human RANKL (receptor activator of nuclear factor kappa-B ligand). Denosumab-nxxp has an approximate molecular weight of 147 kDa and is produced in genetically engineered mammalian (Chinese hamster ovary) cells.

Bildyos (denosumab-nxxp) injection is a sterile, preservative-free, clear to slightly opalescent, colorless to slightly yellow solution for subcutaneous use.

Each 1 mL single-dose prefilled syringe of Bildyos contains 60 mg denosumab-nxxp (60 mg/mL solution), glacial acetic acid (1.02 mg), polysorbate 20 (0.1 mg), sorbitol (47.0 mg), Water for Injection (USP), and sodium hydroxide to a pH of 5.2.

12 CLINICAL PHARMACOLOGY

12.1 Mechanism of Action

Denosumab products bind to RANKL, a transmembrane or soluble protein essential for the formation, function, and survival of osteoclasts, the cells responsible for bone resorption. Denosumab products prevent RANKL from activating its receptor, RANK, on the surface of osteoclasts and their precursors. Prevention of the RANKL/RANK interaction inhibits osteoclast formation, function, and survival, thereby decreasing bone resorption and increasing bone mass and strength in both cortical and trabecular bone.

12.2 Pharmacodynamics

In clinical studies, treatment with 60 mg of denosumab resulted in reduction in the bone resorption marker serum type 1 C-telopeptide (CTX) by approximately 85% by 3 days, with maximal reductions occurring by 1 month. CTX levels were below the limit of assay quantitation (0.049 ng/mL) in 39% to 68% of patients 1 to 3 months after dosing of denosumab. At the end of each dosing interval, CTX reductions were partially attenuated from a maximal reduction of ≥ 87% to ≥ 45% (range: 45% to 80%), as serum denosumab levels diminished, reflecting the reversibility of the effects of denosumab on bone remodeling. These effects were sustained with continued treatment. Upon reinitiation, the degree of inhibition of CTX by denosumab was similar to that observed in patients initiating denosumab treatment.

Consistent with the physiological coupling of bone formation and resorption in skeletal remodeling, subsequent reductions in bone formation markers (i.e., osteocalcin and procollagen type 1 N-terminal peptide [P1NP]) were observed starting 1 month after the first dose of denosumab. After discontinuation of denosumab therapy, markers of bone resorption increased to levels 40% to 60% above pretreatment values but returned to baseline levels within 12 months.

12.3 Pharmacokinetics

In a study conducted in healthy male and female volunteers (n = 73, age range: 18 to 64 years) following a single subcutaneously administered denosumab dose of 60 mg, the mean area-under-the-concentration-time curve up to 16 weeks (AUC0-16 weeks) of denosumab was 316 mcg⋅day/mL (standard deviation [SD] = 101 mcg⋅day/mL). The mean maximum denosumab concentration (Cmax) was 6.75 mcg/mL (SD = 1.89 mcg/mL). No accumulation or change in denosumab pharmacokinetics with time is observed with multiple dosing of 60 mg subcutaneously administered once every 6 months.

Absorption

Following subcutaneous administration, the median time to maximum denosumab concentration (Tmax) was 10 days (range: 3 to 21 days).

Distribution

The mean volume of distribution for denosumab was 5.2 L (SD = 1.7 L).

Elimination

Serum denosumab concentrations declined over a period of 4 to 5 months with a mean half-life of 25.4 days (SD = 8.5 days; n = 46).

A population pharmacokinetic analysis was performed to evaluate the effects of demographic characteristics. This analysis showed no notable differences in pharmacokinetics with age (in postmenopausal women), race, or body weight (36 to 140 kg).

Seminal Fluid Pharmacokinetic Study

Serum and seminal fluid concentrations of denosumab were measured in 12 healthy male volunteers (age range: 43-65 years). After a single 60 mg subcutaneous administration of denosumab, the mean (± SD) Cmaxvalues in the serum and seminal fluid samples were 6170 (± 2070) and 100 (± 81.9) ng/mL, respectively, resulting in a maximum seminal fluid concentration of approximately 2% of serum levels. The median (range) Tmaxvalues in the serum and seminal fluid samples were 8.0 (7.9 to 21) and 21 (8.0 to 49) days, respectively. Among the subjects, the highest denosumab concentration in seminal fluid was 301 ng/mL at 22 days post-dose. On the first day of measurement (10 days post-dose), nine of eleven subjects had quantifiable concentrations in semen. On the last day of measurement (106 days post-dose), five subjects still had quantifiable concentrations of denosumab in seminal fluid, with a mean (± SD) seminal fluid concentration of 21.1 (± 36.5) ng/mL across all subjects (n = 12).

Drug Interactions

In a study of 19 postmenopausal women with low BMD and rheumatoid arthritis treated with etanercept (50 mg subcutaneous injection once weekly), a single-dose of denosumab (60 mg subcutaneous injection) was administered 7 days after the previous dose of etanercept. No clinically significant changes in the pharmacokinetics of etanercept were observed.

Cytochrome P450 substrates

In a study of 17 postmenopausal women with osteoporosis, midazolam (2 mg oral) was administered 2 weeks after a single-dose of denosumab (60 mg subcutaneous injection), which approximates the Tmaxof denosumab. Denosumab did not affect the pharmacokinetics of midazolam, which is metabolized by cytochrome P450 3A4 (CYP3A4). This indicates that denosumab products should not alter the pharmacokinetics of drugs metabolized by CYP3A4 in postmenopausal women with osteoporosis.

Specific Populations

Gender:Mean serum denosumab concentration-time profiles observed in a study conducted in healthy men ≥ 50 years were similar to those observed in a study conducted in postmenopausal women using the same dose regimen.

Age:The pharmacokinetics of denosumab were not affected by age across all populations studied whose ages ranged from 28 to 87 years.

Race:The pharmacokinetics of denosumab were not affected by race.

Renal Impairment:In a study of 55 patients with varying degrees of renal function, including patients on dialysis, the degree of renal impairment had no effect on the pharmacokinetics of denosumab; thus, dose adjustment for renal impairment is not necessary.

Hepatic Impairment:No clinical studies have been conducted to evaluate the effect of hepatic impairment on the pharmacokinetics of denosumab products.

12.6 Immunogenicity

The observed incidence of anti-drug antibodies is highly dependent on the sensitivity and specificity of the assay. Differences in assay methods preclude meaningful comparisons of the incidence of anti-drug antibodies in the studies described below with the incidence of anti-drug antibodies in other studies, including those of denosumab or of other denosumab products.

Using an electrochemiluminescent bridging immunoassay, less than 1% (55 out of 8113) of patients treated with denosumab for up to 5 years tested positive for binding antibodies (including pre-existing, transient, and developing antibodies). None of the patients tested positive for neutralizing antibodies, as was assessed using a chemiluminescent cell-based in vitrobiological assay.

There was no identified clinically significant effect of anti-drug antibodies on pharmacokinetics, pharmacodynamics, safety, or effectiveness of denosumab.

13 NONCLINICAL TOXICOLOGY

13.1 Carcinogenesis, Mutagenesis, Impairment of Fertility

Carcinogenicity

The carcinogenic potential of denosumab products has not been evaluated in long-term animal studies.

Mutagenicity

The genotoxic potential of denosumab products has not been evaluated.

Impairment of Fertility

Denosumab had no effect on female fertility or male reproductive organs in monkeys at doses that were 13- to 50-fold higher than the recommended human dose of 60 mg subcutaneously administered once every 6 months, based on body weight (mg/kg).

13.2 Animal Toxicology and/or Pharmacology

Denosumab products are inhibitors of osteoclastic bone resorption via inhibition of RANKL.

In ovariectomized monkeys, once-monthly treatment with denosumab suppressed bone turnover and increased BMD and strength of cancellous and cortical bone at doses 50-fold higher than the recommended human dose of 60 mg administered once every 6 months, based on body weight (mg/kg). Bone tissue was normal with no evidence of mineralization defects, accumulation of osteoid, or woven bone.

Because the biological activity of denosumab in animals is specific to nonhuman primates, evaluation of genetically engineered (“knockout”) mice or use of other biological inhibitors of the RANK/RANKL pathway, namely OPG-Fc, provided additional information on the pharmacodynamic properties of denosumab products. RANK/RANKL knockout mice exhibited absence of lymph node formation, as well as an absence of lactation due to inhibition of mammary gland maturation (lobulo-alveolar gland development during pregnancy). Neonatal RANK/RANKL knockout mice exhibited reduced bone growth and lack of tooth eruption. A corroborative study in 2-week-old rats given the RANKL inhibitor OPG-Fc also showed reduced bone growth, altered growth plates, and impaired tooth eruption. These changes were partially reversible in this model when dosing with the RANKL inhibitors was discontinued.

14 CLINICAL STUDIES

14.1 Treatment of Postmenopausal Women with Osteoporosis

The efficacy and safety of denosumab in the treatment of postmenopausal osteoporosis was demonstrated in a 3-year, randomized, double-blind, placebo-controlled trial. Enrolled women had a baseline BMD T-score between -2.5 and -4.0 at either the lumbar spine or total hip. Women with other diseases (such as rheumatoid arthritis, osteogenesis imperfecta, and Paget's disease) or on therapies that affect bone were excluded from this study. The 7808 enrolled women were aged 60 to 91 years with a mean age of 72 years. Overall, the mean baseline lumbar spine BMD T-score was -2.8, and 23% of women had a vertebral fracture at baseline. Women were randomized to receive subcutaneous injections of either placebo (N = 3906) or denosumab 60 mg (N = 3902) once every 6 months. All women received at least 1000 mg calcium and 400 IU vitamin D supplementation daily.

The primary efficacy variable was the incidence of new morphometric (radiologically-diagnosed) vertebral fractures at 3 years. Vertebral fractures were diagnosed based on lateral spine radiographs (T4-L4) using a semiquantitative scoring method. Secondary efficacy variables included the incidence of hip fracture and nonvertebral fracture, assessed at 3 years.

Effect on Vertebral Fractures

Denosumab significantly reduced the incidence of new morphometric vertebral fractures at 1, 2, and 3 years (p < 0.0001), as shown in Table 3. The incidence of new vertebral fractures at year 3 was 7.2% in the placebo-treated women compared to 2.3% for the denosumab-treated women. The absolute risk reduction was 4.8% and relative risk reduction was 68% for new morphometric vertebral fractures at year 3.

Table 3. The Effect of Denosumab on the Incidence of New Vertebral Fractures in Postmenopausal Women
 | Proportion of Women with Fracture (%)^+ |  | Absolute Risk Reduction (%)*(95% CI) | Relative Risk Reduction (%)* (95% CI)
 | Placebo N = 3691 (%) | Denosumab N = 3702 (%) | Absolute Risk Reduction (%)*(95% CI) | Relative Risk Reduction (%)* (95% CI)
0-1 Year | 2.2 | 0.9 | 1.4 (0.8, 1.9) | 61 (42, 74)
0-2 Years | 5.0 | 1.4 | 3.5 (2.7, 4.3) | 71 (61, 79)
0-3 Years | 7.2 | 2.3 | 4.8 (3.9, 5.8) | 68 (59, 74)
^+Event rates based on crude rates in each interval.
* Absolute risk reduction and relative risk reduction based on Mantel-Haenszel method adjusting for age group variable.

Denosumab was effective in reducing the risk for new morphometric vertebral fractures regardless of age, baseline rate of bone turnover, baseline BMD, baseline history of fracture, or prior use of a drug for osteoporosis.

Effect on Hip Fractures

The incidence of hip fracture was 1.2% for placebo-treated women compared to 0.7% for denosumab-treated women at year 3. The age-adjusted absolute risk reduction of hip fractures was 0.3% with a relative risk reduction of 40% at 3 years (p = 0.04) (see Figure 1).

Figure 1. Cumulative Incidence of Hip Fractures Over 3 Years

N = Number of subjects randomized

Effect on Nonvertebral Fractures

Treatment with denosumab resulted in a significant reduction in the incidence of nonvertebral fractures (see Table 4).

Table 4. The Effect of Denosumab on the Incidence of Nonvertebral Fractures at Year 3
 | Proportion of Women with Fracture (%)^+ |  | Absolute Risk Reduction (%) (95% CI) | Relative Risk Reduction (%) (95% CI)
 | Placebo N = 3906 (%) | Denosumab N = 3902 (%) | Absolute Risk Reduction (%) (95% CI) | Relative Risk Reduction (%) (95% CI)
Nonvertebral fracture^1 | 8.0 | 6.5 | 1.5 (0.3, 2.7) | 20 (5, 33) *
^+Event rates based on Kaplan-Meier estimates at 3 years.
^1Excluding those of the vertebrae (cervical, thoracic, and lumbar), skull, facial, mandible, metacarpus, and finger and toe phalanges.
* p-value = 0.01.

Effect on Bone Mineral Density (BMD)

Treatment with denosumab significantly increased BMD at all anatomic sites measured at 3 years. The treatment differences in BMD at 3 years were 8.8% at the lumbar spine, 6.4% at the total hip, and 5.2% at the femoral neck. Consistent effects on BMD were observed at the lumbar spine, regardless of baseline age, race, weight/body mass index (BMI), baseline BMD, and level of bone turnover.

After denosumab discontinuation, BMD returned to approximately baseline levels within 12 months.

Bone Histology and Histomorphometry

A total of 115 transiliac crest bone biopsy specimens were obtained from 92 postmenopausal women with osteoporosis at either month 24 and/or month 36 (53 specimens in denosumab group, 62 specimens in placebo group). Of the biopsies obtained, 115 (100%) were adequate for qualitative histology and 7 (6%) were adequate for full quantitative histomorphometry assessment.

Qualitative histology assessments showed normal architecture and quality with no evidence of mineralization defects, woven bone, or marrow fibrosis in patients treated with denosumab.

The presence of double tetracycline labeling in a biopsy specimen provides an indication of active bone remodeling, while the absence of tetracycline label suggests suppressed bone formation. In patients treated with denosumab, 35% had no tetracycline label present at the month 24 biopsy and 38% had no tetracycline label present at the month 36 biopsy, while 100% of placebo-treated patients had double label present at both time points. When compared to placebo, treatment with denosumab resulted in virtually absent activation frequency and markedly reduced bone formation rates. However, the long-term consequences of this degree of suppression of bone remodeling are unknown.

14.2 Treatment to Increase Bone Mass in Men with Osteoporosis

The efficacy and safety of denosumab in the treatment to increase bone mass in men with osteoporosis was demonstrated in a 1-year, randomized, double-blind, placebo-controlled trial. Enrolled men had a baseline BMD T-score between -2.0 and -3.5 at the lumbar spine or femoral neck. Men with a BMD T-score between -1.0 and -3.5 at the lumbar spine or femoral neck were also enrolled if there was a history of prior fragility fracture. Men with other diseases (such as rheumatoid arthritis, osteogenesis imperfecta, and Paget's disease) or on therapies that may affect bone were excluded from this study. The 242 men enrolled in the study ranged in age from 31 to 84 years with a mean age of 65 years. Men were randomized to receive SC injections of either placebo (n = 121) or denosumab 60 mg (n = 121) once every 6 months. All men received at least 1000 mg calcium and at least 800 IU vitamin D supplementation daily.

Effect on Bone Mineral Density (BMD)

The primary efficacy variable was percent change in lumbar spine BMD from baseline to 1-year. Secondary efficacy variables included percent change in total hip, and femoral neck BMD from baseline to 1-year.

Treatment with denosumab significantly increased BMD at 1-year. The treatment differences in BMD at 1-year were 4.8% (+0.9% placebo, +5.7% denosumab; (95% CI: 4.0, 5.6); p < 0.0001) at the lumbar spine, 2.0% (+0.3% placebo, +2.4% denosumab) at the total hip, and 2.2% (0.0% placebo, +2.1% denosumab) at femoral neck. Consistent effects on BMD were observed at the lumbar spine regardless of baseline age, race, BMD, testosterone concentrations, and level of bone turnover.

Bone Histology and Histomorphometry

A total of 29 transiliac crest bone biopsy specimens were obtained from men with osteoporosis at 12 months (17 specimens in denosumab group, 12 specimens in placebo group). Of the biopsies obtained, 29 (100%) were adequate for qualitative histology and, in denosumab patients, 6 (35%) were adequate for full quantitative histomorphometry assessment. Qualitative histology assessments showed normal architecture and quality with no evidence of mineralization defects, woven bone, or marrow fibrosis in patients treated with denosumab. The presence of double tetracycline labeling in a biopsy specimen provides an indication of active bone remodeling, while the absence of tetracycline label suggests suppressed bone formation. In patients treated with denosumab, 6% had no tetracycline label present at the month 12 biopsy, while 100% of placebo-treated patients had double label present. When compared to placebo, treatment with denosumab resulted in markedly reduced bone formation rates. However, the long-term consequences of this degree of suppression of bone remodeling are unknown.

14.3 Treatment of Glucocorticoid-Induced Osteoporosis

The efficacy and safety of denosumab in the treatment of patients with glucocorticoid-induced osteoporosis was assessed in the 12-month primary analysis of a 2-year, randomized, multicenter, double-blind, parallel-group, active-controlled study (NCT 01575873) of 795 patients (70% women and 30% men) aged 20 to 94 years (mean age of 63 years) treated with greater than or equal to 7.5 mg/day oral prednisone (or equivalent) for < 3 months prior to study enrollment and planning to continue treatment for a total of at least 6 months (glucocorticoid-initiating subpopulation; n = 290) or ≥ 3 months prior to study enrollment and planning to continue treatment for a total of at least 6 months (glucocorticoid-continuing subpopulation, n = 505). Enrolled patients < 50 years of age were required to have a history of osteoporotic fracture. Enrolled patients ≥ 50 years of age who were in the glucocorticoid-continuing subpopulation were required to have a baseline BMD T-score of ≤ -2.0 at the lumbar spine, total hip, or femoral neck; or a BMD T-score ≤ -1.0 at the lumbar spine, total hip, or femoral neck and a history of osteoporotic fracture.

Patients were randomized (1:1) to receive either an oral daily bisphosphonate (active-control, risedronate 5 mg once daily) (n = 397) or denosumab 60 mg subcutaneously once every 6 months (n = 398) for one year. Randomization was stratified by gender within each subpopulation. Patients received at least 1000 mg calcium and 800 IU vitamin D supplementation daily.

Effect on Bone Mineral Density (BMD)

In the glucocorticoid-initiating subpopulation, denosumab significantly increased lumbar spine BMD compared to the active-control at one year (Active-control 0.8%, denosumab 3.8%) with a treatment difference of 2.9% (p < 0.001). In the glucocorticoid-continuing subpopulation, denosumab significantly increased lumbar spine BMD compared to active-control at one year (Active-control 2.3%, denosumab 4.4%) with a treatment difference of 2.2% (p < 0.001). Consistent effects on lumbar spine BMD were observed regardless of gender; race; geographic region; menopausal status; and baseline age, lumbar spine BMD T-score, and glucocorticoid dose within each subpopulation.

Bone Histology

Bone biopsy specimens were obtained from 17 patients (11 in the active-control treatment group and 6 in the denosumab treatment group) at Month 12. Of the biopsies obtained, 17 (100%) were adequate for qualitative histology. Qualitative assessments showed bone of normal architecture and quality without mineralization defects or bone marrow abnormality. The presence of double tetracycline labeling in a biopsy specimen provides an indication of active bone remodeling, while the absence of tetracycline label suggests suppressed bone formation. In patients treated with active-control, 100% of biopsies had tetracycline label. In patients treated with denosumab, 1 (33%) had tetracycline label and 2 (67%) had no tetracycline label present at the 12 -month biopsy. Evaluation of full quantitative histomorphometry including bone remodeling rates was not possible in the glucocorticoid-induced osteoporosis population treated with denosumab. The long-term consequences of this degree of suppression of bone remodeling in glucocorticoid-treated patients is unknown.

14.4 Treatment of Bone Loss in Men with Prostate Cancer

The efficacy and safety of denosumab in the treatment of bone loss in men with nonmetastatic prostate cancer receiving androgen deprivation therapy (ADT) were demonstrated in a 3-year, randomized (1:1), double-blind, placebo-controlled, multinational study. Men less than 70 years of age had either a BMD T-score at the lumbar spine, total hip, or femoral neck between -1.0 and -4.0, or a history of an osteoporotic fracture. The mean baseline lumbar spine BMD T-score was -0.4, and 22% of men had a vertebral fracture at baseline. The 1468 men enrolled ranged in age from 48 to 97 years (median 76 years). Men were randomized to receive subcutaneous injections of either placebo (n = 734) or denosumab 60 mg (n = 734) once every 6 months for a total of 6 doses. Randomization was stratified by age (< 70 years vs. ≥ 70 years) and duration of ADT at trial entry (≤ 6 months vs. > 6 months). Seventy-nine percent of patients received ADT for more than 6 months at study entry. All men received at least 1000 mg calcium and 400 IU vitamin D supplementation daily.

Effect on Bone Mineral Density (BMD)

The primary efficacy variable was percent change in lumbar spine BMD from baseline to month 24. An additional key secondary efficacy variable was the incidence of new vertebral fracture through month 36 diagnosed based on x-ray evaluation by two independent radiologists. Lumbar spine BMD was higher at 2 years in denosumab-treated patients as compared to placebo-treated patients [-1.0% placebo, +5.6% denosumab; treatment difference 6.7% (95% CI: 6.2, 7.1); p < 0.0001].

With approximately 62% of patients followed for 3 years, treatment differences in BMD at 3 years were 7.9% (-1.2% placebo, +6.8% denosumab) at the lumbar spine, 5.7% (-2.6% placebo, +3.2% denosumab) at the total hip, and 4.9% (-1.8% placebo, +3.0% denosumab) at the femoral neck. Consistent effects on BMD were observed at the lumbar spine in relevant subgroups defined by baseline age, BMD, and baseline history of vertebral fracture.

Effect on Vertebral Fractures

Denosumab significantly reduced the incidence of new vertebral fractures at 3 years (p = 0.0125), as shown in Table 5.

Table 5. The Effect of Denosumab on the Incidence of New Vertebral Fractures in Men with Nonmetastatic Prostate Cancer
 | Proportion of Men with Fracture (%)^+ |  | Absolute Risk Reduction (%)* (95% CI) | Relative Risk Reduction (%)* (95% CI)
 | Placebo N = 673 (%) | Denosumab N = 679 (%) | Absolute Risk Reduction (%)* (95% CI) | Relative Risk Reduction (%)* (95% CI)
0-1 Year | 1.9 | 0.3 | 1.6 (0.5, 2.8) | 85 (33, 97)
0-2 Years | 3.3 | 1.0 | 2.2 (0.7, 3.8) | 69 (27, 86)
0-3 Years | 3.9 | 1.5 | 2.4 (0.7, 4.1) | 62 (22, 81)
^+Event rates based on crude rates in each interval.
* Absolute risk reduction and relative risk reduction based on Mantel-Haenszel method adjusting for age group and ADT duration variables.

14.5 Treatment of Bone Loss in Women with Breast Cancer

The efficacy and safety of denosumab in the treatment of bone loss in women receiving adjuvant aromatase inhibitor (AI) therapy for breast cancer was assessed in a 2-year, randomized (1:1), double-blind, placebo-controlled, multinational study. Women had baseline BMD T-scores between -1.0 to -2.5 at the lumbar spine, total hip, or femoral neck, and had not experienced fracture after age 25. The mean baseline lumbar spine BMD T-score was -1.1, and 2.0% of women had a vertebral fracture at baseline. The 252 women enrolled ranged in age from 35 to 84 years (median 59 years). Women were randomized to receive subcutaneous injections of either placebo (n = 125) or denosumab 60 mg (n = 127) once every 6 months for a total of 4 doses. Randomization was stratified by duration of adjuvant AI therapy at trial entry (≤ 6 months vs. > 6 months). Sixty-two percent of patients received adjuvant AI therapy for more than 6 months at study entry. All women received at least 1000 mg calcium and 400 IU vitamin D supplementation daily.

Effect on Bone Mineral Density (BMD)

The primary efficacy variable was percent change in lumbar spine BMD from baseline to month 12. Lumbar spine BMD was higher at 12 months in denosumab-treated patients as compared to placebo-treated patients [-0.7% placebo, +4.8% denosumab; treatment difference 5.5% (95% CI: 4.8, 6.3); p < 0.0001].

With approximately 81% of patients followed for 2 years, treatment differences in BMD at 2 years were 7.6% (-1.4% placebo, +6.2% denosumab) at the lumbar spine, 4.7% (-1.0% placebo, +3.8% denosumab) at the total hip, and 3.6% (-0.8% placebo, +2.8% denosumab) at the femoral neck.

16 HOW SUPPLIED/STORAGE AND HANDLING

How Supplied

Bildyos (denosumab-nxxp) injection is a clear to slightly opalescent, colorless to slightly yellow solution for subcutaneous administration.
Each Bildyos single-dose prefilled syringe contains 60 mg/mL of denosumab in a 1 mL single-dose syringe with a 29 gauge 1/2 inch needle with a BD UltraSafe PlusTM passive safety guard;

The prefilled syringe with safety guard is not made with natural rubber latex.

60 mg/mL in a single-dose prefilled syringe | 1 per carton | NDC 78206-193-01

Storage and Handling

Store Bildyos refrigerated at 2°C to 8°C (36°F to 46°F) in the original carton to protect from light. Do not freeze. Prior to administration, Bildyos may be allowed to reach room temperature up to 25°C (77°F) in the original container. Once removed from the refrigerator, Bildyos must not be exposed to temperatures above 25°C (77°F) and must be used within 30 days. Discard Bildyos if not used within the 30 days.

Do not use Bildyos after the expiry date printed on the label.

Protect Bildyos from direct light and heat.

Avoid vigorous shaking of Bildyos.

17 PATIENT COUNSELING INFORMATION

Advise the patient to read the FDA-approved patient labeling (Medication Guide).

Hypocalcemia

Advise the patient to adequately supplement with calcium and vitamin D and instruct them on the importance of maintaining serum calcium levels while receiving Bildyos [see Warnings and Precautions (5.1), Use in Specific Populations (8.6)] . Advise patients to seek prompt medical attention if they develop signs or symptoms of hypocalcemia.

Severe Hypocalcemia in Patients with Advanced Chronic Kidney Disease

Advise patients with advanced chronic kidney disease, including those who are dialysis-dependent, about the symptoms of hypocalcemia and the importance of maintaining serum calcium levels with adequate calcium and activated vitamin D supplementation. Advise these patients to have their serum calcium measured weekly for the first month after Bildyos administration and monthly thereafter [see Dosage and Administration (2.2), Warnings and Precautions (5.1), Use in Specific Populations (8.6)].

Drug Products with Same Active Ingredient

Advise patients that if they receive Bildyos, they should not receive other denosumab products concomitantly [see Warnings and Precautions (5.2)] .

Hypersensitivity

Advise patients to seek prompt medical attention if signs or symptoms of hypersensitivity reactions occur. Advise patients who have had signs or symptoms of systemic hypersensitivity reactions that they should not receive denosumab products [see Warnings and Precautions (5.3), Contraindications (4)] .

Osteonecrosis of the Jaw

Advise patients to maintain good oral hygiene during treatment with Bildyos and to inform their dentist prior to dental procedures that they are receiving Bildyos. Patients should inform their physician or dentist if they experience persistent pain and/or slow healing of the mouth or jaw after dental surgery [see Warnings and Precautions (5.4)] .

Atypical Subtrochanteric and Diaphyseal Femoral Fractures

Advise patients to report new or unusual thigh, hip, or groin pain [see Warnings and Precautions (5.5)].

Multiple Vertebral Fractures (MVF) Following Treatment Discontinuation

Advise patients not to interrupt Bildyos therapy without talking to their physician [see Warnings and Precautions (5.6)].

Serious Infections

Advise patients to seek prompt medical attention if they develop signs or symptoms of infections, including cellulitis [see Warnings and Precautions (5.7)] .

Dermatologic Adverse Reactions

Advise patients to seek prompt medical attention if they develop signs or symptoms of dermatological reactions (such as dermatitis, rashes, and eczema) [see Warnings and Precautions (5.8)] .

Musculoskeletal Pain

Inform patients that severe bone, joint, and/or muscle pain have been reported in patients taking denosumab products. Patients should report severe symptoms if they develop [see Warnings and Precautions (5.9)] .

Pregnancy/Nursing

Counsel females of reproductive potential to use effective contraceptive measure to prevent pregnancy during treatment and for at least 5 months after the last dose of Bildyos. Advise the patient to contact their physician immediately if pregnancy does occur during these times. Advise patients not to take Bildyos while pregnant or breastfeeding. If a patient wishes to start breastfeeding after treatment, advise her to discuss the appropriate timing with her physician [see Contraindications (4), Use in Specific Populations (8.1)] .

Schedule of Administration

Advise patients that if a dose of Bildyos is missed, the injection should be administered as soon as convenient. Thereafter, schedule injections every 6 months from the date of the last injection.

Bildyos (denosumab-nxxp)

Manufactured by:

Shanghai Henlius Biotech, Inc.
Room 901, 9th Floor, Building 1, No. 367 Shengrong Road, China (Shanghai) Pilot Free Trade Zone.

U.S. License No. 2354

Manufactured for:
Organon LLC, a subsidiary of

ORGANON & Co.,
Jersey City, NJ 07302, USA.

PROLIA®is a registered trademark of Amgen Inc.

BD UltraSafe PlusTMis a trademark of Becton, Dickinson and Company.

MEDICATION GUIDE
BILDYOS®[bil' dee ose]
(denosumab-nxxp)
Injection, for subcutaneous use

What is the most important information I should know about Bildyos?
If you receive Bildyos, you should not receive other denosumab products at the same time.
Bildyos can cause serious side effects including:

- Increased risk of severe low calcium levels in your blood (hypocalcemia).Bildyos may lower the calcium levels in your blood. If you have low blood calcium before you start receiving Bildyos, it may get worse during treatment. Your low blood calcium must be treated before you receive Bildyos. Talk to your doctor before starting Bildyos. Your doctor may prescribe calcium and vitamin D to help prevent low calcium levels in your blood while you take Bildyos. Take calcium and vitamin D as your doctor tells you to.
  If you have advanced chronic kidney disease (may or may not be on kidney dialysis), Bildyos may increase your risk for severe low calcium levels in your blood, which could result in hospitalization, life-threatening events and death. A mineral and bone disorder associated with kidney disease called chronic kidney disease-mineral bone disorder (CKD-MBD) may increase your risk for severe low calcium levels in blood. Before you start Bildyos and during treatment, your doctor may need to do certain blood tests to check for CKD-MBD.
  Most people with low blood calcium levels do not have symptoms, but some people may have symptoms. Call your doctor right away if you have symptoms of low blood calcium such as:
  - spasms, twitches, or cramps in your muscles
  - numbness or tingling in your fingers, toes, or around your mouth
- Serious allergic reactions. Serious allergic reactions have happened in people who take denosumab products. Call your doctor or go to your nearest emergency room right away if you have any symptoms of a serious allergic reaction. Symptoms of a serious allergic reaction may include:
  - low blood pressure (hypotension)
  - trouble breathing
  - throat tightness
  - swelling of your face, lips, or tongue
  - rash
  - itching
  - hives
- Severe jaw bone problems (osteonecrosis).Severe jaw bone problems may happen when you take Bildyos. Your doctor should examine your mouth before you start Bildyos. Your doctor may tell you to see your dentist before you start Bildyos. It is important for you to practice good mouth care during treatment with Bildyos. Ask your doctor or dentist about good mouth care if you have any questions.
- Unusual thigh bone fractures.Some people have developed unusual fractures in their thigh bone. Symptoms of a fracture include new or unusual pain in your hip, groin, or thigh.
- Increased risk of broken bones, including broken bones in the spine, after stopping, skipping or delaying Bildyos.Talk with your doctor before starting Bildyos treatment. After your treatment with Bildyos is stopped, or if you skip or delay taking a dose, your risk for breaking bones, including bones in your spine, is increased. Your risk for having more than 1 broken bone in your spine is increased if you have already had a broken bone in your spine. Do not stop, skip or delay taking Bildyos without first talking with your doctor. If your Bildyos treatment is stopped, talk to your doctor about other medicine that you can take.
- Serious infections.Serious infections in your skin, lower stomach area (abdomen), bladder, or ear may happen if you take Bildyos. Inflammation of the inner lining of the heart (endocarditis) due to an infection also may happen more often in people who take Bildyos. You may need to go to the hospital for treatment if you develop an infection.
  Bildyos is a medicine that may affect the ability of your body to fight infections. People who have a weakened immune system or take medicines that affect the immune system may have an increased risk for developing serious infections. Call your doctor right away if you have any of the following symptoms of infection:
  - fever or chills
  - skin that looks red or swollen and is hot or tender to touch
  - fever, shortness of breath, cough that will not go away
  - severe abdominal pain
  - frequent or urgent need to urinate or burning feeling when you urinate
- Skin problems. Skin problems such as inflammation of your skin (dermatitis), rash, and eczema may happen if you take Bildyos. Call your doctor if you have any of the following symptoms of skin problems that do not go away or get worse:
  - redness
  - itching
  - small bumps or patches (rash)
  - your skin is dry or feels like leather
  - blisters that ooze or become crusty
  - skin peeling
- Bone, joint, or muscle pain.Some people who take denosumab products develop severe bone, joint, or muscle pain.

Call your doctor right away if you have any of these side effects.

What is Bildyos?
Bildyos is a prescription medicine used to:

- Treat osteoporosis (thinning and weakening of bone) in women after menopause (“change of life”) who:
  - are at high risk for fracture (broken bone)
  - cannot use another osteoporosis medicine or other osteoporosis medicines did not work well
- Increase bone mass in men with osteoporosis who are at high risk for fracture.
- Treat osteoporosis in men and women who will be taking corticosteroid medicines (such as prednisone) for at least 6 months and are at high risk for fracture.
- Treat bone loss in men who are at high risk for fracture receiving certain treatments for prostate cancer that has not spread to other parts of the body.
- Treat bone loss in women who are at high risk for fracture receiving certain treatments for breast cancer that has not spread to other parts of the body.

It is not known if Bildyos is safe and effective in children. Bildyos is not approved for use in children.

Do not take Bildyos if you:

- have been told by your doctor that your blood calcium level is too low.
- are pregnant or plan to become pregnant.
- are allergic to denosumab products or any of the ingredients in Bildyos. See the end of this Medication Guide for a complete list of ingredients in Bildyos.

Before taking Bildyos, tell your doctor about all of your medical conditions, including if you:

- are taking other denosumab products.
- have low blood calcium.
- cannot take daily calcium and vitamin D.
- had parathyroid or thyroid surgery (glands located in your neck).
- have been told you have trouble absorbing minerals in your stomach or intestines (malabsorption syndrome).
- have kidney problems or are on kidney dialysis.
- are taking medicine that can lower your blood calcium levels.
- plan to have dental surgery or teeth removed.
- are pregnant or plan to become pregnant. Bildyos may harm your unborn baby.
  Females who are able to become pregnant:
  - Your healthcare provider should do a pregnancy test before you start treatment with Bildyos.
  - You should use an effective method of birth control (contraception) during treatment with Bildyos and for at least 5 months after your last dose of Bildyos.
  - Tell your doctor right away if you become pregnant while taking Bildyos.
- are breastfeeding or plan to breastfeed. It is not known if Bildyos passes into your breast milk. You and your doctor should decide if you will take Bildyos or breastfeed. You should not do both.

Tell your doctor about all the medicines you take,including prescription and over-the-counter medicines, vitamins, and herbal supplements.
Know the medicines you take. Keep a list of medicines with you to show to your doctor or pharmacist when you get a new medicine.

How will I receive Bildyos?

- Bildyos is an injection that will be given to you by a healthcare provider. Bildyos is injected under your skin (subcutaneous).
- You will receive Bildyos 1 time every 6 months.
- You should take calcium and vitamin D as your doctor tells you to while you receive Bildyos.
- If you miss a dose of Bildyos, you should receive your injection as soon as you can.
- Take good care of your teeth and gums while you receive Bildyos. Brush and floss your teeth regularly.
- Tell your dentist that you are receiving Bildyos before you have dental work.

What are the possible side effects of Bildyos?
Bildyos may cause serious side effects.

- See “ What is the most important information I should know about Bildyos?”
- It is not known if the use of Bildyos over a long period of time may cause slow healing of broken bones.

The most common side effects of Bildyos in women who are being treated for osteoporosis after menopause are:

- back pain
- pain in your arms and legs
- high cholesterol

- muscle pain
- bladder infection

The most common side effects of Bildyos in men with osteoporosis are:

- back pain
- joint pain

- common cold (runny nose or sore throat)

The most common side effects of Bildyos in patients with glucocorticoid-induced osteoporosis are:

- back pain
- high blood pressure

- lung infection (bronchitis)
- headache

The most common side effects of Bildyos in patients receiving certain treatments for prostate or breast cancer are:

- joint pain
- back pain

- pain in your arms and legs
- muscle pain

Tell your doctor if you have any side effect that bothers you or that does not go away.
These are not all the possible side effects of Bildyos.
Call your doctor for medical advice about side effects. You may report side effects to FDA at 1-800-FDA-1088.

How should I store Bildyos if I need to pick it up from a pharmacy?

- Keep Bildyos in a refrigerator at 36°F to 46°F (2°C to 8°C) in the original carton.
- Do not freeze Bildyos.
- When you remove Bildyos from the refrigerator, Bildyos must be kept at room temperature [up to 77°F (25°C)] in the original carton and must be used within 30 days.
- Do not keep Bildyos at temperatures above 77°F (25°C). Warm temperatures will affect how Bildyos works.
- Do not shake Bildyos.
- Keep Bildyos in the original carton to protect from light.

Keep Bildyos and all medicines out of the reach of children.

General information about the safe and effective use of Bildyos.
Medicines are sometimes prescribed for purposes other than those listed in a Medication Guide. Do not use Bildyos for a condition for which it was not prescribed. Do not give Bildyos to other people, even if they have the same symptoms that you have. It may harm them. You can ask your doctor or pharmacist for information about Bildyos that is written for healthcare providers.

What are the ingredients in Bildyos?
Active ingredient:denosumab-nxxp
Inactive ingredients:glacial acetic acid, polysorbate 20, sodium hydroxide, sorbitol, Water for Injection (USP).

Manufactured by:

Shanghai Henlius Biotech, Inc.
Room 901, 9th Floor, Building 1, No. 367 Shengrong Road, China (Shanghai) Pilot Free Trade Zone.
U.S. License No. 2354

Manufactured for:

Organon LLC, a subsidiary of

ORGANON & Co.,
Jersey City, NJ 07302, USA.
For more information, go to www. Bildyos.com or call Organon LLC. at 1-844-674-3200.

This Medication Guide has been approved by the U.S. Food and Drug Administration.

Issued: 08/2025